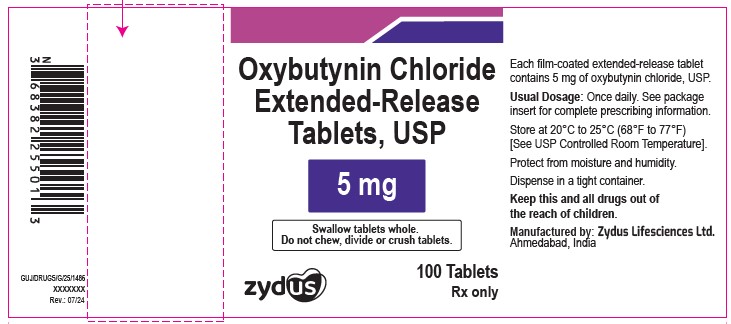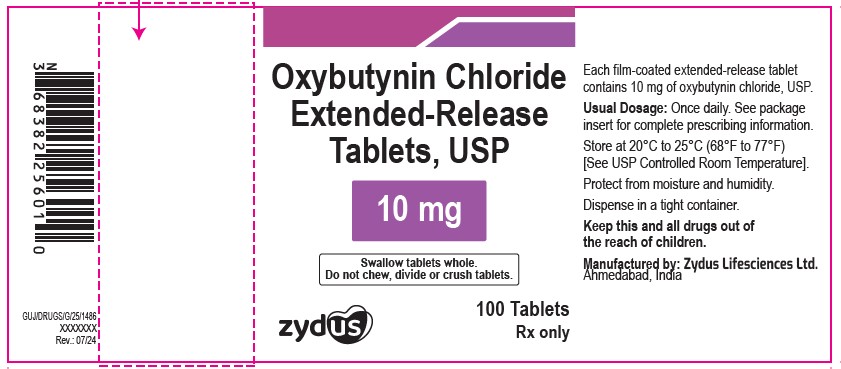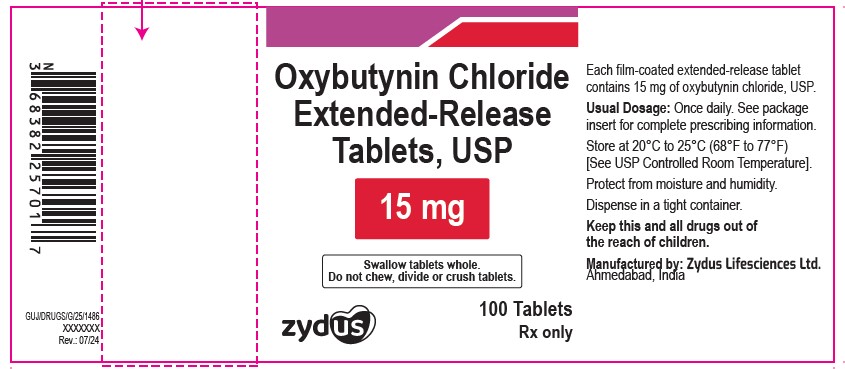 DRUG LABEL: oxybutynin
NDC: 70771-1086 | Form: TABLET, FILM COATED, EXTENDED RELEASE
Manufacturer: Zydus Lifesciences Limited
Category: prescription | Type: HUMAN PRESCRIPTION DRUG LABEL
Date: 20241203

ACTIVE INGREDIENTS: OXYBUTYNIN CHLORIDE 5 mg/1 1
INACTIVE INGREDIENTS: ALGINIC ACID; HYDROGENATED CASTOR OIL; HYPROMELLOSES; LACTOSE MONOHYDRATE; MAGNESIUM STEARATE; METHACRYLIC ACID; CELLULOSE, MICROCRYSTALLINE; POVIDONE; TALC; TRIETHYL CITRATE

OXYBUTYNIN CHLORIDE EXTENDED-RELEASE TABLETS

PACKAGE LABEL.PRINCIPAL DISPLAY PANEL

Oxybutynin chloride extended-release tablets USP, 5 mg

NDC 70771-1086-1

100 tablets

Rx only

Oxybutynin chloride extended-release tablets USP, 10 mg

NDC 70771-1087-1

100 tablets

Rx only

Oxybutynin chloride extended-release tablets USP, 15 mg

NDC 70771-1088-1

100 tablets

Rx only